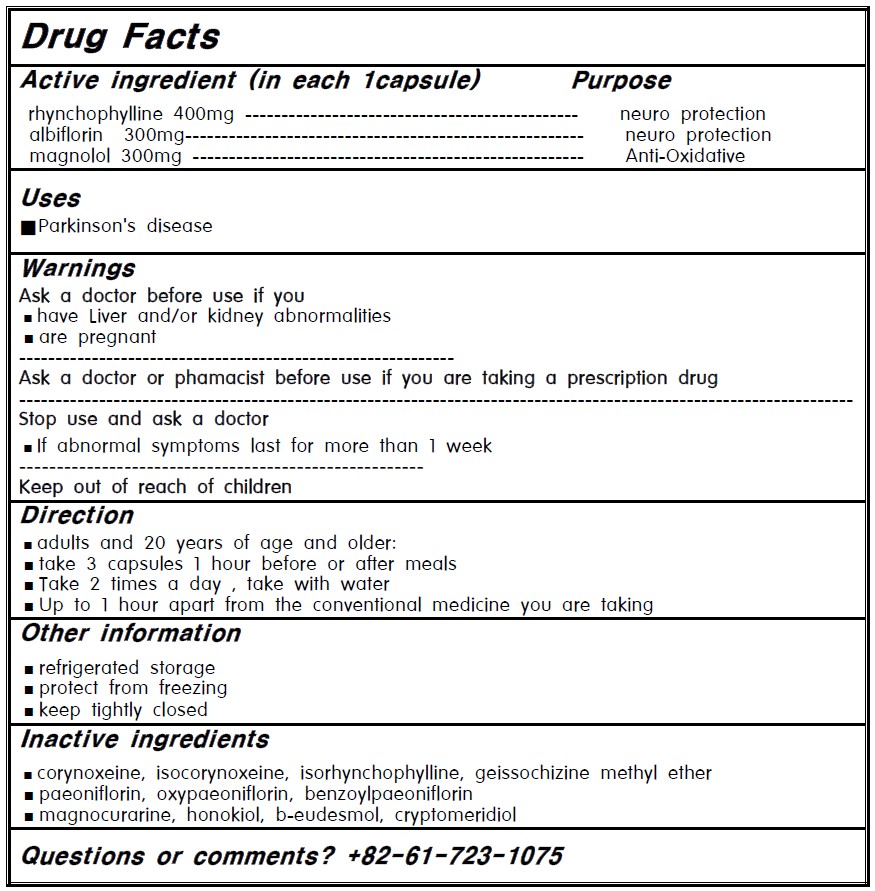 DRUG LABEL: Hepad S5
NDC: 82049-201 | Form: CAPSULE
Manufacturer: YOUNGJIN Korean Medicine Clinic
Category: otc | Type: HUMAN OTC DRUG LABEL
Date: 20231220

ACTIVE INGREDIENTS: RHYNCHOPHYLLINE 40 g/100 g; MAGNOLOL 30 g/100 g
INACTIVE INGREDIENTS: .BETA.-EUDESMOL; OXYPAEONIFLORA; ISOCORYNOXEINE; ISORHYNCHOPHYLLINE; HONOKIOL; PEONIFLORIN; PROXIMADIOL; CORYNOXEINE

82049-201

Active ingredient

rhynchophylline 400mg

albiflorin 300mg

magnolol 300mg

Purpose

neuro protection

neuro protection

Anti-Oxidative

Uses

- Parkinson's disease

Warnings

Ask a doctor before use if you

- have Liver and/or kidney abnormalities
- are pregnant

Ask a doctor or phamacist before use

if you are taking a prescription drug

Stop use and ask a doctor

- If abnormal symptoms last for more than 1 week

Keep out of reach of children

Direction

- adults and 20 years of age and older:
- take 3 capsules 1 hour before or after meals
- Take 2 times a day , take with water
- Up to 1 hour apart from the conventional medicine you are taking

Other information

- refrigerated storage
- protect from freezing
- keep tightly closed

Inactive ingredients

- corynoxeine, isocorynoxeine, isorhynchophylline, geissochizine methyl ether
- paeoniflorin, oxypaeoniflorin, benzoylpaeoniflorin
- magnocurarine, honokiol, b-eudesmol, cryptomeridiol